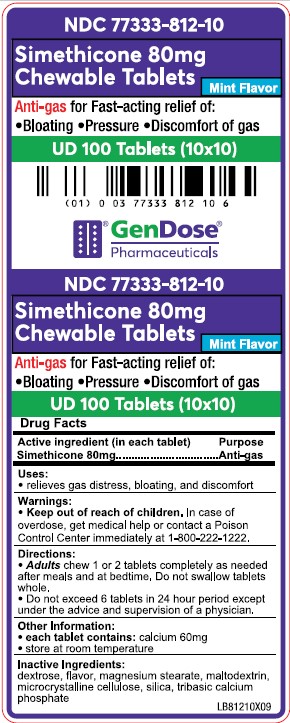 DRUG LABEL: SIMETHICONE 80MG
NDC: 77333-812 | Form: TABLET, CHEWABLE
Manufacturer: Gendose Pharmaceuticals, LLC
Category: otc | Type: HUMAN OTC DRUG LABEL
Date: 20240108

ACTIVE INGREDIENTS: DIMETHICONE 80 mg/1 1
INACTIVE INGREDIENTS: MAGNESIUM STEARATE; DEXTROSE; MALTODEXTRIN; TRIBASIC CALCIUM PHOSPHATE; MICROCRYSTALLINE CELLULOSE; SILICON DIOXIDE

GENDOSE - SIMETHICONE 80 mg CHEWABLE TABLETS (77333-812)

ACTIVE INGREDIENT (IN EACH TABLET)

SIMETHICONE 80MG

PURPOSE

ANTI-GAS

USES

- RELIEVES GAS DISTRESS, BLOATING, AND DISCOMFORT

WARNINGS

- GET MEDICAL HELP OR CONTACT A POISON CONTROL CENTER IMMEDIATELY AT 1-800-222-1222.

KEEP OUT OF REACH OF CHILDREN.

DIRECTIONS

- ADULTS CHEW 1 OR 2 TABLETS COMPLETELY AS NEEDED AFTER MEALS AND AT BEDTIME. DO NOT SWALLOW TABLETS WHOLE.
- DO NOT EXCEED 6 TABLETS IN 24 HOUR PERIOD EXCEPT UNDER THE ADVICE AND SUPERVISION OF A PHYSICIAN.

OTHER INFORMATION

- EACH TABLET CONTAINS: CALCIUM 60MG
- STORE AT ROOM TEMPERATURE

INACTIVE INGREDIENTS

DEXTROSE, FLAVOR, MAGNESIUM STEARATE, MALTODEXTRIN, MICROCRYSTALLINE CELLULOSE, SILICA, TRIBASIC CALCIUM PHOSPHATE